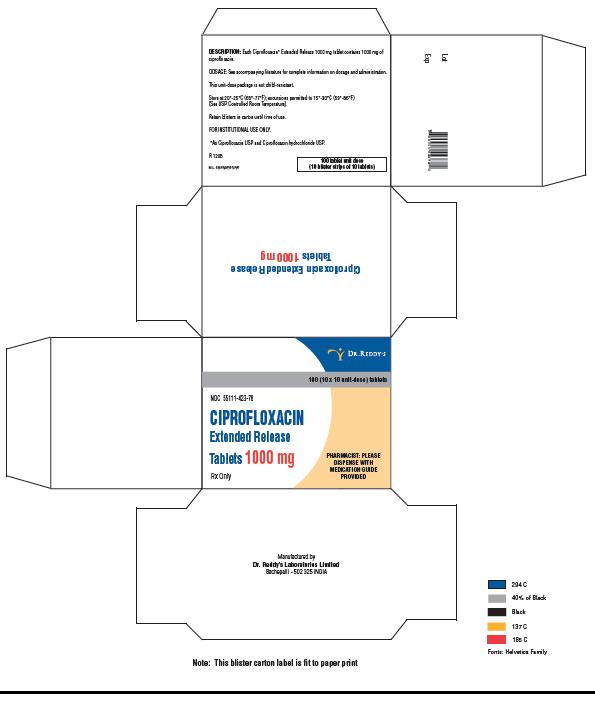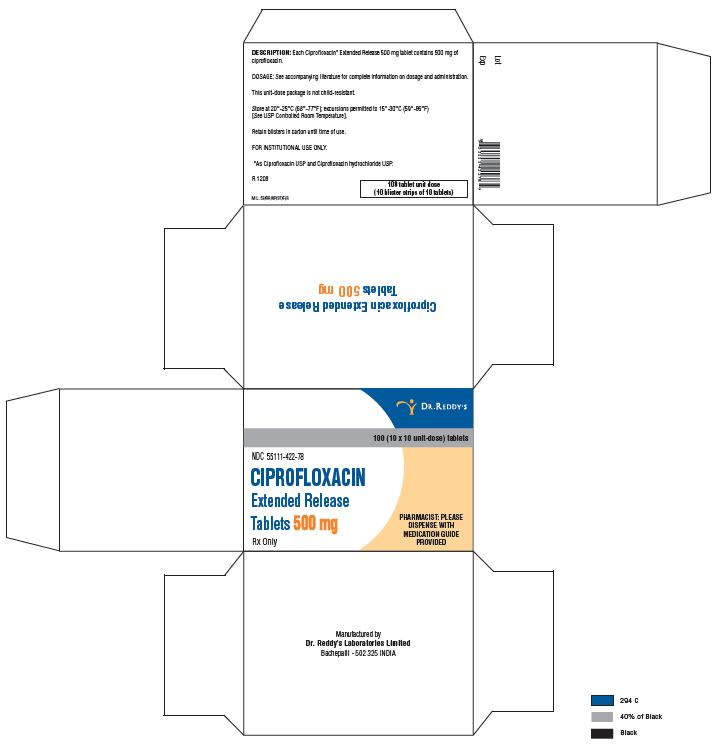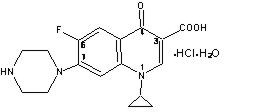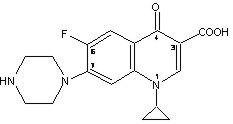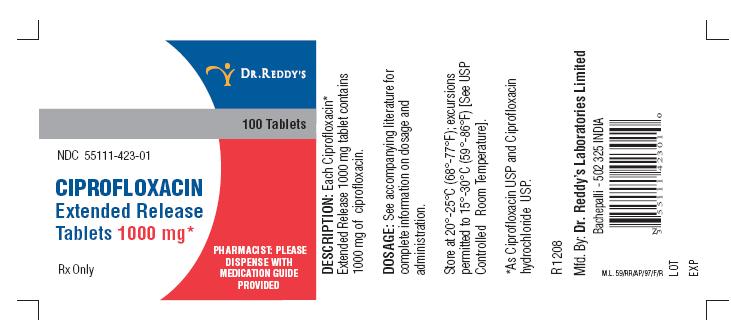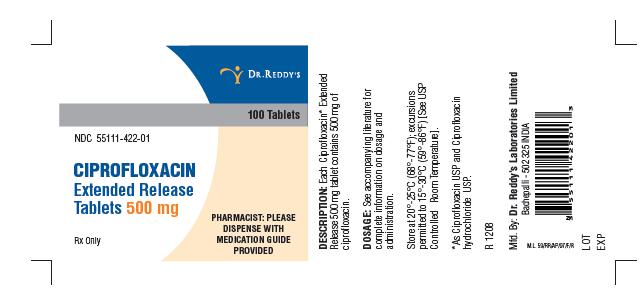 DRUG LABEL: Ciprofloxacin
NDC: 55111-422 | Form: TABLET, FILM COATED, EXTENDED RELEASE
Manufacturer: Dr. Reddy's Laboratories Limited
Category: prescription | Type: HUMAN PRESCRIPTION DRUG LABEL
Date: 20110830

ACTIVE INGREDIENTS: ciprofloxacin hydrochloride 287.5 mg/1 1; ciprofloxacin 212.6 mg/1 1
INACTIVE INGREDIENTS: crospovidone; SILICON DIOXIDE; ethylcelluloses; hypromelloses; magnesium stearate; POLYETHYLENE GLYCOL 400; succinic acid; titanium dioxide

Ciprofloxacin Extended-Release Tablets

BOXED WARNING

WARNING: Fluoroquinolones, including ciprofloxacin, are associated with an increased risk of tendinitis and tendon rupture in all ages. This risk is further increased in older patients usually over 60 years of age, in patients taking corticosteroid drugs, and in patients with kidney, heart or lung transplants (See WARNINGS).

Fluoroquinolones, including ciprofloxacin, may exacerbate muscle weakness in persons with myasthenia gravis. Avoid ciprofloxacin in patients with known history of myasthenia gravis (see WARNINGS).

To reduce the development of drug-resistant bacteria and maintain the effectiveness of ciprofloxacin extended-release tablets and other antibacterial drugs, ciprofloxacin extended-release tablets should be used only to treat or prevent infections that are proven or strongly suspected to be caused by bacteria.

DESCRIPTION

Ciprofloxacin [as ciprofloxacin and ciprofloxacin hydrochloride] extended-release tablets contains ciprofloxacin, a synthetic broad-spectrum antimicrobial agent for oral administration. Ciprofloxacin extended-release tablets are coated, bilayer tablets consisting of an immediate-release layer and matrix type controlled-release layer. The tablets contain a combination of two types of ciprofloxacin drug substance, ciprofloxacin hydrochloride, USP and ciprofloxacin, USP. Ciprofloxacin hydrochloride is 1-cyclopropyl-6-fluoro-1,4-dihydro-4-oxo-7-(1-piperazinyl)-3-quinolinecarboxylic acid hydrochloride. It is provided as monohydrate. The empirical formula of the monohydrate is C17H18FN3O3 • HCl • H2O and its molecular weight is 385.8. The drug substance is a faintly yellowish to light yellow crystalline substance. The chemical structure of the monohydrate is as follows:

Ciprofloxacin, USP is 1-cyclopropyl-6-fluoro-1, 4-dihydro-4-oxo-7-(1-piperazinyl)-3-quinolinecarboxylic acid. As the anhydrous form, its empirical formula is C17H18FN3O3 and its molecular weight is 331.34. It is a pale yellowish to light yellow crystalline substance and its chemical structure is as follows:

Ciprofloxacin extended-release tablets are available in 500 mg and 1000 mg (ciprofloxacin equivalent) tablet strength. Ciprofloxacin extended-release tablets are white to off white, film coated, oblong shaped, biconvex tablets. Each ciprofloxacin extended-release 500 mg tablet contains 500 mg of ciprofloxacin as ciprofloxacin HCl (287.5 mg, calculated as ciprofloxacin on anhydrous basis) and ciprofloxacin (212.6 mg, calculated on the dried basis) Each ciprofloxacin extended-release 1000 mg tablet contains 1000 mg of ciprofloxacin as ciprofloxacin HCl (574.9 mg, calculated as ciprofloxacin on anhydrous basis) and ciprofloxacin (425.2 mg, calculated on the dried basis). The inactive ingredients are crospovidone, colloidal silicon dioxide, ethylcellulose, hypromellose, magnesium stearate, polyethylene glycol, succinic acid and titanium dioxide

CLINICAL PHARMACOLOGY

Absorption

Ciprofloxacin extended-release tablets are formulated to release drug at a slower rate compared to immediate-release tablets. Approximately 35% of the dose is contained within an immediate-release component, while the remaining 65% is contained in a slow-release matrix.

Maximum plasma ciprofloxacin concentrations are attained between 1 and 4 hours after dosing with ciprofloxacin extended-release tablets. In comparison to the 250 mg and 500 mg ciprofloxacin immediate-release BID treatment, the Cmax of ciprofloxacin extended-release tablets 500 mg and 1000 mg once daily are higher than the corresponding BID doses, while the AUCs over 24 hours are equivalent.

The following table compares the pharmacokinetic parameters obtained at steady state for these four treatment regimens (500 mg QD ciprofloxacin extended-release tablets versus 250 mg BID ciprofloxacin immediate-release tablets and 1000 mg QD ciprofloxacin extended-release tablets versus 500 mg BID ciprofloxacin immediate-release).

Ciprofloxacin Pharmacokinetics (Mean ± SD) Following Ciprofloxacin Tablets and Ciprofloxacin Extended-Release Tablets Administration
 | Cmax (mg/L) | AUC0-24h (mg∙h/L) | T1/2 (hr) | Tmax (hr) [median (range)]
Ciprofloxacin extended-release tablets 500 mg QD | 1.59 ± 0.43 | 7.97 ± 1.87 | 6.6 ± 1.4 | 1.5 (1.0 – 2.5)
Ciprofloxacin tablets 250 mg BID | 1.14 ± 0.23 | 8.25 ± 2.15 | 4.8 ± 0.6 | 1.0 (0.5 – 2.5)
Ciprofloxacin extended-release tablets 1000 mg QD | 3.11 ± 1.08 | 16.83 ± 5.65 | 6.31 ± 0.72 | 2.0 (1 – 4)
Ciprofloxacin tablets 500 mg BID | 2.06 ± 0.41 | 17.04 ± 4.79 | 5.66 ± 0.89 | 2.0 (0.5 – 3.5)

Results of the pharmacokinetic studies demonstrate that ciprofloxacin extended-release tablets may be administered with or without food (e.g. high-fat and low-fat meals or under fasted conditions).

Distribution

The volume of distribution calculated for intravenous ciprofloxacin is approximately 2.1 – 2.7 L/kg. Studies with the oral and intravenous forms of ciprofloxacin have demonstrated penetration of ciprofloxacin into a variety of tissues. The binding of ciprofloxacin to serum proteins is 20% to 40%, which is not likely to be high enough to cause significant protein binding interactions with other drugs. Following administration of a single dose of ciprofloxacin extended-release tablets, ciprofloxacin concentrations in urine collected up to 4 hours after dosing averaged over 300 mg/L for both the 500 mg and 1000 mg tablets; in urine excreted from 12 to 24 hours after dosing, ciprofloxacin concentration averaged 27 mg/L for the 500 mg tablet, and 58 mg/L for the 1000 mg tablet.

Metabolism

Four metabolites of ciprofloxacin were identified in human urine. The metabolites have antimicrobial activity, but are less active than unchanged ciprofloxacin. The primary metabolites are oxociprofloxacin (M3) and sulfociprofloxacin (M2), each accounting for roughly 3% to 8% of the total dose. Other minor metabolites are desethylene ciprofloxacin (M1), and formylciprofloxacin (M4). The relative proportion of drug and metabolite in serum corresponds to the composition found in urine. Excretion of these metabolites was essentially complete by 24 hours after dosing. Ciprofloxacin is an inhibitor of human cytochrome P450 1A2 (CYP1A2) mediated metabolism. Coadministration of ciprofloxacin with other drugs primarily metabolized by CYP1A2 results in increased plasma concentrations of these drugs and could lead to clinically significant adverse events of the coadministered drug (see CONTRAINDICATIONS; WARNINGS; PRECAUTIONS: Drug Interactions).

Elimination

The elimination kinetics of ciprofloxacin are similar for the immediate-release and the ciprofloxacin extended-release tablet. In studies comparing the ciprofloxacin extended-release and immediate-release ciprofloxacin, approximately 35% of an orally administered dose was excreted in the urine as unchanged drug for both formulations. The urinary excretion of ciprofloxacin is virtually complete within 24 hours after dosing. The renal clearance of ciprofloxacin, which is approximately 300 mL/minute, exceeds the normal glomerular filtration rate of 120 mL/minute. Thus, active tubular secretion would seem to play a significant role in its elimination. Co-administration of probenecid with immediate-release ciprofloxacin results in about a 50% reduction in the ciprofloxacin renal clearance and a 50% increase in its concentration in the systemic circulation. Although bile concentrations of ciprofloxacin are several fold higher than serum concentrations after oral dosing with the immediate-release tablet, only a small amount of the dose administered is recovered from the bile as unchanged drug. An additional 1% to 2% of the dose is recovered from the bile in the form of metabolites. Approximately 20% to 35% of an oral dose of immediate-release ciprofloxacin is recovered from the feces within 5 days after dosing. This may arise from either biliary clearance or transintestinal elimination.

Special Populations

Pharmacokinetic studies of the immediate-release oral tablet (single dose) and intravenous (single and multiple dose) forms of ciprofloxacin indicate that plasma concentrations of ciprofloxacin are higher in elderly subjects (> 65 years) as compared to young adults. Cmax is increased 16% to 40%, and mean AUC is increased approximately 30%, which can be at least partially attributed to decreased renal clearance in the elderly. Elimination half-life is only slightly (~20%) prolonged in the elderly. These differences are not considered clinically significant. (See PRECAUTIONS, Geriatric Use.)

In patients with reduced renal function, the half-life of ciprofloxacin is slightly prolonged. No dose adjustment is required for patients with uncomplicated urinary tract infections receiving 500 mg ciprofloxacin extended-release tablets. For complicated urinary tract infection and acute uncomplicated pyelonephritis, where 1000 mg is the appropriate dose, the dosage of ciprofloxacin extended-release tablets should be reduced to ciprofloxacin extended-release tablets 500 mg q24h in patients with creatinine clearance below 30 mL/min. (See DOSAGE AND ADMINISTRATION.)

In studies in patients with stable chronic cirrhosis, no significant changes in ciprofloxacin pharmacokinetics have been observed. The kinetics of ciprofloxacin in patients with acute hepatic insufficiency, however, have not been fully elucidated. (See DOSAGE AND ADMINISTRATION.)

Drug-Drug Interactions

Concomitant administration with tizanidine is contraindicated. (See CONTRAINDICATIONS). Previous studies with immediate-release ciprofloxacin have shown that concomitant administration of ciprofloxacin with theophylline decreases the clearance of theophylline resulting in elevated serum theophylline levels and increased risk of a patient developing CNS or other adverse reactions. Ciprofloxacin also decreases caffeine clearance and inhibits the formation of paraxanthine after caffeine administration. Absorption of ciprofloxacin is significantly reduced by concomitant administration of multivalent cation-containing products such as magnesium/aluminum antacids, sucralfate, VIDEX® (didanosine) chewable/buffered tablets or pediatric powder, or products containing calcium, iron, or zinc. (See WARNINGS: PRECAUTIONS, Drug Interactions and Information for Patients, and DOSAGE AND ADMINISTRATION.)

Antacids

When ciprofloxacin extended-release tablets given as a single 1000 mg dose was administered two hours before, or four hours after a magnesium/aluminum-containing antacid (900 mg aluminum hydroxide and 600 mg magnesium hydroxide as a single oral dose) to 18 healthy volunteers, there was a 4% and 19% reduction, respectively, in the mean Cmax of ciprofloxacin. The reduction in the mean AUC was 24% and 26%, respectively. Ciprofloxacin extended-release tablets should be administered at least 2 hours before or 6 hours after antacids containing magnesium or aluminum, as well as sucralfate, VIDEX® (didanosine) chewable/buffered tablets or pediatric powder, other highly buffered drugs, metal cations such as iron, and multivitamin preparations with zinc. Although ciprofloxacin extended-release tablets may be taken with meals that include milk, concomitant administration with dairy products or with calcium-fortified juices alone should be avoided, since decreased absorption is possible. (See PRECAUTIONS, Information for Patients and Drug Interactions, and DOSAGE AND ADMINISTRATION.)

Omeprazole

When ciprofloxacin extended-release tablets was administered as a single 1000 mg dose concomitantly with omeprazole (40 mg once daily for three days) to 18 healthy volunteers, the mean AUC and Cmax of ciprofloxacin were reduced by 20% and 23%, respectively. The clinical significance of this interaction has not been determined. (See PRECAUTIONS, Drug Interactions.)

MICROBIOLOGY

Mechanism of Action

The bactericidal action of ciprofloxacin results from inhibition of topoisomerase II (DNA gyrase) and topoisomerase IV (both Type II topoisomerases), which are required for bacterial DNA replication, transcription, repair, and recombination.

Drug ResistanceThe mechanism of action of fluoroquinolones, including ciprofloxacin, is different from that of other antimicrobial agents such as beta-lactams, macrolides, tetracyclines, or aminoglycosides; therefore, microorganisms resistant to these classes of drugs may be susceptible to ciprofloxacin. There is no known cross-resistance between ciprofloxacin and other classes of antimicrobials. Resistance to ciprofloxacin in vitro develops slowly (multiple-step mutation). Resistance to ciprofloxacin due to spontaneous mutations occurs at a general frequency of between < 10^-9 to 1x10^-6.

Activity in vitro and in vivo

Ciprofloxacin has in vitro activity against a wide range of gram-negative and gram-positive microorganisms. Ciprofloxacin is slightly less active when tested at acidic pH. The inoculum size has little effect when tested in vitro. The minimal bactericidal concentration (MBC) generally does not exceed the minimal inhibitory concentration (MIC) by more than a factor of 2.

Ciprofloxacin has been shown to be active against most strains of the following microorganisms, both in vitro and in clinical infections as described in the INDICATIONS AND USAGE section of the package insert for ciprofloxacin extended-release tablets..

Aerobic gram-positive microorganisms
Enterococcus faecalis (Many strains are only moderately susceptible.)
Staphylococcus saprophyticus

Aerobic gram-negative microorganisms
Escherichia coli
Klebsiella pneumoniae
Proteus mirabilis
Pseudomonas aeruginosa

The following in vitro data are available, but their clinical significance is unknown.

Ciprofloxacin exhibits in vitro minimum inhibitory concentrations (MICs) of 1 µg/mL or less against most (≥ 90%) strains of the following microorganisms; however, the safety and effectiveness of ciprofloxacin extended-release tablets in treating clinical infections due to these microorganisms have not been established in adequate and well-controlled clinical trials.

Aerobic gram-negative microorganisms
Citrobacter koseri Morganella morganii
Citrobacter freundii Proteus vulgaris
Edwardsiella tarda Providencia rettgeri
Enterobacter aerogenes Providencia stuartii
Enterobacter cloacae Serratia marcescens
Klebsiella oxytoca

Susceptibility Tests

- Dilution Techniques:

Quantitative methods are used to determine antimicrobial minimal inhibitory concentrations (MICs). These MICs provide estimates of the susceptibility of bacteria to antimicrobial compounds. The MICs should be determined using a standardized procedure. Standardized procedures are based on a dilution method^1 (broth or agar) or equivalent with standardized inoculum concentrations and standardized concentrations of ciprofloxacin. The MIC values should be interpreted according to the criteria outlined in Table 1.

- Diffusion Techniques:

Quantitative methods that require measurement of zone diameters also provide reproducible estimates of the susceptibility of bacteria to antimicrobial compounds. One such standardized procedure^2 requires the use of standardized inoculum concentrations. This procedure uses paper disks impregnated with 5-µg ciprofloxacin to test the susceptibility of microorganisms to ciprofloxacin.

Reports from the laboratory providing results of the standard single-disk susceptibility test with a 5-µg ciprofloxacin disk should be interpreted according to the criteria outlined in Table 1. Interpretation involves correlation of the diameter obtained in the disk text with the MIC for ciprofloxacin.

Table 1: Susceptibility Interpretive Criteria for Ciprofloxacin
Species | MIC (μg/mL) |  |  | Zone Diameter (mm)
Species | S | I | R | S | I | R
Enterobacteriacae | ≤1 | 2 | ≥4 | ≥21 | 16-20 | ≤15
Enterococcus faecalis | ≤1 | 2 | ≥4 | ≥21 | 16-20 | ≤15
Pseudomonas aeruginosa | ≤1 | 2 | ≥4 | ≥21 | 16-20 | ≤15
Staphylococcus saprophyticus | ≤1 | 2 | ≥4 | ≥21 | 16-20 | ≤15

S=Susceptible, I=Intermediate, and R=Resistant.

A report of “Susceptible” indicates that the pathogen is likely to be inhibited if the antimicrobial compound in the blood reaches the concentrations usually achievable. A report of “Intermediate” indicates that the result should be considered equivocal, and, if the microorganism is not fully susceptible to alternative, clinically feasible drugs, the test should be repeated. This category implies possible clinical applicability in body sites where the drug is physiologically concentrated or in situations where high dosage of drug can be used. This category also provides a buffer zone which prevents small uncontrolled technical factors from causing major discrepancies in interpretation. A report of “Resistant” indicates that the pathogen is not likely to be inhibited if the antimicrobial compound in the blood reaches the concentrations usually achievable; other therapy should be selected.

• Quality Control: Standardized susceptibility test procedures require the use of laboratory control microorganisms to control the technical aspects of the laboratory procedures. Standard ciprofloxacin powder should provide the following MIC values according to criteria outlined in Table 2. For the diffusion technique, the 5-μg ciprofloxacin disk should provide the zone diameters outlined in Table 2.

Table 2: Quality Control for Susceptibility Testing
Strains | MIC range (μg/mL) | Zone Diameter (mm)
Enterococcus faecalis ATCC 29212 | 0.25-2 | -
Escherichia coli ATCC 25922 | 0.004-0.015 | 30-40
Pseudomonas aeruginosa ATCC 27853 | 0.25-1.0 | 25-33
Staphylococcus aureus ATCC29212 | 0.12-0.5 | -
Staphylococcus aureus ATCC25923 | - | 22-30

INDICATIONS AND USAGE

Ciprofloxacin extended-release tablets are indicated only for the treatment of urinary tract infections, including acute uncomplicated pyelonephritis, caused by susceptible strains of the designated microorganisms as listed below. Ciprofloxacin extended-release tablets and ciprofloxacin immediate-release tablets are not interchangeable. Please see DOSAGE AND ADMINISTRATION for specific recommendations.

Uncomplicated Urinary Tract Infections (Acute Cystitis) caused by Escherichia coli, Proteus mirabilis, Enterococcus faecalis, or Staphylococcus saprophyticus [Treatment of infections due to this organism in the organ system was studied in fewer than 10 patients.] .

Complicated Urinary Tract Infections caused by Escherichia coli, Klebsiella pneumoniae, Enterococcus faecalis, Proteus mirabilis, or Pseudomonas aeruginosa .

Acute Uncomplicated Pyelonephritis caused by Escherichia coli.

THE SAFETY AND EFFICACY OF CIPROFLOXACIN EXTENDED-RELEASE TABLETS IN TREATING INFECTIONS OTHER THAN URINARY TRACT INFECTIONS HAS NOT BEEN DEMONSTRATED.

Appropriate culture and susceptibility tests should be performed before treatment in order to isolate and identify organisms causing infection and to determine their susceptibility to ciprofloxacin. Therapy with ciprofloxacin extended-release tablets may be initiated before results of these tests are known; once results become available appropriate therapy should be continued. Culture and susceptibility testing performed periodically during therapy will provide information not only on the therapeutic effect of the antimicrobial agent but also on the possible emergence of bacterial resistance.

To reduce the development of drug-resistant bacteria and maintain the effectiveness of ciprofloxacin extended-release tablets and other antibacterial drugs, ciprofloxacin extended-release tablets should be used only to treat or prevent infections that are proven or strongly suspected to be caused by susceptible bacteria. When culture and susceptibility information are available, they should be considered in selecting or modifying antibacterial therapy. In the absence of such data, local epidemiology and susceptibility patterns may contribute to the empiric selection of therapy.

CONTRAINDICATIONS

Ciprofloxacin extended-release tablets are contraindicated in persons with a history of hypersensitivity to ciprofloxacin, any member of the quinolone class of antimicrobial agents, or any of the product components.

Concomitant administration with tizanidine is contraindicated. (See PRECAUTIONS: Drug Interactions.)

WARNINGS

Tendinopathy and Tendon Rupture:

Fluoroquinolones, including ciprofloxacin extended-release tablets, are associated with an increased risk of tendinitis and tendon rupture in all ages. This adverse reaction most frequently involves the Achilles tendon, and rupture of the Achilles tendon may require surgical repair. Tendinitis and tendon rupture in the rotator cuff (the shoulder), the hand, the biceps, the thumb, and other tendon sites have also been reported. The risk of developing fluoroquinolone-associated tendinitis and tendon rupture is further increased in older patients usually over 60 years of age, in patients taking corticosteroid drugs, and in patients with kidney, heart or lung transplants. Factors, in addition to age and corticosteroid use, that may independently increase the risk of tendon rupture include strenuous physical activity, renal failure, and previous tendon disorders such as rheumatoid arthritis. Tendinitis and tendon rupture have also occurred in patients taking fluoroquinolones who do not have the above risk factors. Tendon rupture can occur during or after completion of therapy; cases occurring up to several months after completion of therapy have been reported. Ciprofloxacin extended-release tablets should be discontinued if the patient experiences pain, swelling, inflammation or rupture of a tendon. Patients should be advised to rest at the first sign of tendinitis or tendon rupture, and to contact their healthcare provider regarding changing to a non-quinolone antimicrobial drug.

Exacerbation of Myasthenia Gravis: Fluoroquinolones, including ciprofloxacin extended-release tablets, have neuromuscular blocking activity and may exacerbate muscle weakness in persons with myasthenia gravis. Postmarketing serious adverse events, including deaths and requirement for ventilatory support, have been associated with fluoroquinolone use in persons with myasthenia gravis. Avoid ciprofloxacin extended-release tablets in patients with known history of myasthenia gravis. (See PRECAUTIONS: Information for Patientsand ADVERSEREACTIONS: Post-Marketing Adverse Event Reports).

THE SAFETY AND EFFECTIVENESS OF CIPROFLOXACIN EXTENDED-RELEASE TABLETS IN PEDIATRIC PATIENTS AND ADOLESCENTS (UNDER THE AGE OF 18 YEARS), PREGNANT WOMEN, AND NURSING WOMEN HAVE NOT BEEN ESTABLISHED. (See PRECAUTIONS: Pediatric Use, Pregnancy,and Nursing Motherssubsections.) The oral administration of ciprofloxacin caused lameness in immature dogs. Histopathological examination of the weight-bearing joints of these dogs revealed permanent lesions of the cartilage. Related quinolone-class drugs also produce erosions of cartilage of weight-bearing joints and other signs of arthropathy in immature animals of various species.(See ANIMALPHARMACOLOGY.)

Cytochrome P450 (CYP450)

Ciprofloxacin is an inhibitor of the hepatic CYP1A2 enzyme pathway. Coadministration of ciprofloxacin and other drugs primarily metabolized by CYP1A2 (e.g. theophylline, methylxanthines, tizanidine) results in increased plasma concentrations of the coadministered drug and could lead to clinically significant pharmacodynamic side effects of the coadministered drug.

Convulsions, increased intracranial pressure, and toxic psychosis have been reported in patients receiving quinolones, including ciprofloxacin. Ciprofloxacin may also cause central nervous system (CNS) events including: dizziness, confusion, tremors, hallucinations, depression, and, rarely, suicidal thoughts or acts. These reactions may occur following the first dose. If these reactions occur in patients receiving ciprofloxacin, the drug should be discontinued and appropriate measures instituted. As with all quinolones, ciprofloxacin should be used with caution in patients with known or suspected CNS disorders that may predispose to seizures or lower the seizure threshold (e.g. severe cerebral arteriosclerosis, epilepsy), or in the presence of other risk factors that may predispose to seizures or lower the seizure threshold (e.g. certain drug therapy, renal dysfunction). (See PRECAUTIONS: General, Information for Patients, Drug Interactions and ADVERSE REACTIONS.)

SERIOUS AND FATAL REACTIONS HAVE BEEN REPORTED IN PATIENTS RECEIVING CONCURRENT ADMINISTRATION OF CIPROFLOXACIN AND THEOPHYLLINE. These reactions have included cardiac arrest, seizure, status epilepticus, and respiratory failure. Although similar serious adverse effects have been reported in patients receiving theophylline alone, the possibility that these reactions may be potentiated by ciprofloxacin cannot be eliminated. If concomitant use cannot be avoided, serum levels of theophylline should be monitored and dosage adjustments made as appropriate.

Serious and occasionally fatal hypersensitivity (anaphylactic) reactions, some following the first dose, have been reported in patients receiving quinolone therapy. Some reactions were accompanied by cardiovascular collapse, loss of consciousness, tingling, pharyngeal or facial edema, dyspnea, urticaria, and itching. Only a few patients had a history of hypersensitivity reactions. Serious anaphylactic reactions require immediate emergency treatment with epinephrine. Oxygen, intravenous steroids, and airway management, including intubation, should be administered as indicated.

Other serious and sometimes fatal events, some due to hypersensitivity, and some due to uncertain etiology, have been reported rarely in patients receiving therapy with quinolones, including ciprofloxacin. These events may be severe and generally occur following the administration of multiple doses. Clinical manifestations may include one or more of the following:

- fever, rash, or severe dermatologic reactions (e.g., toxic epidermal necrolysis, Stevens-Johnson syndrome);
- vasculitis; arthralgia; myalgia; serum sickness;
- allergic pneumonitis;
- interstitial nephritis; acute renal insufficiency or failure;
- hepatitis; jaundice; acute hepatic necrosis or failure;
- anemia, including hemolytic and aplastic; thrombocytopenia, including thrombotic thrombocytopenic purpura; leukopenia; agranulocytosis; pancytopenia; and/or other hematologic abnormalities.

The drug should be discontinued immediately at the first appearance of a skin rash, jaundice, or any other sign of hypersensitivity and supportive measures instituted (See PRECAUTIONS: Information for Patients and ADVERSE REACTIONS).

Clostridium difficile associated diarrhea (CDAD) has been reported with use of nearly all antibacterial agents, including CIPRO, and may range in severity from mild diarrhea to fatal colitis. Treatment with antibacterial agents alters the normal flora of the colon leading to overgrowth of C. difficile.

C. difficile produces toxins A and B which contribute to the development of CDAD. Hypertoxin producing strains of C. difficile cause increased morbidity and mortality, as these infections can be refractory to antimicrobial therapy and may require colectomy. CDAD must be considered in all patients who present with diarrhea following antibiotic use. Careful medical history is necessary since CDAD has been reported to occur over two months after the administration of antibacterial agents.

If CDAD is suspected or confirmed, ongoing antibiotic use not directed against C. difficile may need to be discontinued. Appropriate fluid and electrolyte management, protein supplementation, antibiotic treatment of C. difficile, and surgical evaluation should be instituted as clinically indicated.

Peripheral Neuropathy

Rare cases of sensory or sensorimotor axonal polyneuropathy affecting small and/or large axons resulting in paresthesias, hypoesthesias, dysesthesias and weakness have been reported in patients receiving quinolones, including ciprofloxacin. Ciprofloxacin should be discontinued if the patient experiences symptoms of neuropathy including pain, burning, tingling, numbness, and/or weakness, or is found to have deficits in light touch, pain, temperature, position sense, vibratory sensation, and/or motor strength in order to prevent the development of an irreversible condition.

PRECAUTIONS

General

Crystals of ciprofloxacin have been observed rarely in the urine of human subjects but more frequently in the urine of laboratory animals, which is usually alkaline. (See ANIMAL PHARMACOLOGY.) Crystalluria related to ciprofloxacin has been reported only rarely in humans because human urine is usually acidic. Alkalinity of the urine should be avoided in patients receiving ciprofloxacin. Patients should be well hydrated to prevent the formation of highly concentrated urine.

Quinolones, including ciprofloxacin, may also cause central nervous system (CNS) events, including: nervousness, agitation, insomnia, anxiety, nightmares or paranoia. (See WARNINGS, Information for Patients, and Drug Interactions.)

Photosensitivity/Phototoxicity

Moderate to severe photosensitivity/phototoxicity reactions, the latter of which may manifest as exaggerated sunburn reactions (e.g., burning, erythema, exudation, vesicles, blistering, edema) involving areas exposed to light (typically the face, "V" area of the neck, extensor surfaces of the forearms, dorsa of the hands), can be associated with the use of quinolones after sun or UV light exposure. Therefore, excessive exposure to these sources of light should be avoided. Drug therapy should be discontinued if phototoxicity occurs (See ADVERSE REACTIONS and ADVERSE REACTIONS/ Post-Marketing Adverse Events).

Prescribing ciprofloxacin extended-release tablets in the absence of a proven or strongly suspected bacterial infection or a prophylactic indication is unlikely to provide benefit to the patient and increases the risk of the development of drug-resistant bacteria.

Information for Patients

Patients should be advised:

- to contact their healthcare provider if they experience pain, swelling, or inflammation of a tendon, or weakness or inability to use one of their joints; rest and refrain from exercise; and discontinue ciprofloxacin extended-release tablets treatment.The risk of severe tendon disorder with fluoroquinolones is higher in older patients usually over 60 years of age, in patients taking corticosteroid drugs, and in patients with kidney, heart or lung transplants.
- that fluoroquinolones like ciprofloxacin extended-release tablets may cause worsening of myasthenia gravis symptoms, including muscle weakness and breathing problems. Patients should call their healthcare provider right away if they have any worsening muscle weakness or breathing problems.
- that antibacterial drugs including ciprofloxacin extended-release tablets should only be used to treat bacterial infections. They do not treat viral infections (e.g., the common cold). When ciprofloxacin extended-release tablets is prescribed to treat a bacterial infection, patients should be told that although it is common to feel better early in the course of therapy, the medication should be taken exactly as directed. Skipping doses or not completing the full course of therapy may (1) decrease the effectiveness of the immediate treatment and (2) increase the likelihood that bacteria will develop resistance and will not be treatable by ciprofloxacin extended-release tablets or other antibacterial drugs in the future.
- that ciprofloxacin extended-release tablets may be taken with or without meals and to drink fluids liberally. As with other quinolones, concurrent administration with magnesium/aluminum antacids, or sucralfate, VIDEX® (didanosine) chewable/buffered tablets or pediatric powder, other highly buffered drugs, or with other products containing calcium, iron, or zinc should be avoided. Ciprofloxacin extended-release tablets may be taken two hours before or six hours after taking these products. (See CLINICAL PHARMACOLOGY, Drug-drug Interactions, DOSAGE AND ADMINISTRATION, and PRECAUTIONS, Drug Interactions.) Ciprofloxacin extended-release tablets should not be taken with dairy products (like milk or yogurt) or calcium-fortified juices alone since absorption of ciprofloxacin may be significantly reduced; however, ciprofloxacin extended-release tablets may be taken with a meal that contains these products. (See CLINICAL PHARMACOLOGY, Drug-drug Interactions, DOSAGE AND ADMINISTRATION, and PRECAUTIONS, Drug Interactions.)
- if the patient should forget to take ciprofloxacin extended-release tablets at the usual time, he/she may take the dose later in the day. Do not take more than one ciprofloxacin extended-release tablet per day even if a patient misses a dose. Swallow the ciprofloxacin extended-release tablet whole. DO NOT SPLIT, CRUSH, OR CHEW THE TABLET.
- that ciprofloxacin may be associated with hypersensitivity reactions, even following a single dose, and to discontinue ciprofloxacin extended-release tablets at the first sign of a skin rash or other allergic reaction.
- that photosensitivity/phototoxicity has been reported in patients receiving quinolones. Patients should minimize or avoid exposure to natural or artificial sunlight (tanning beds or UVA/B treatment) while taking quinolones. If patients need to be outdoors while using quinolones, they should wear loose-fitting clothes that protect skin from sun exposure and discuss other sun protection measures with their physician. If a sunburn-like reaction or skin eruption occurs, patients should contact their physician.
- that peripheral neuropathies have been associated with ciprofloxacin use. If symptoms of peripheral neuropathy including pain, burning, tingling, numbness and/or weakness develop, they should discontinue treatment and contact their physicians.
- that ciprofloxacin extended-release tablets may cause dizziness and lightheadedness; therefore, patients should know how they react to this drug before they operate an automobile or machinery or engage in activities requiring mental alertness or coordination.
- that ciprofloxacin increases the effects of tizanidine (Zanaflex®). Patients should not use ciprofloxacin if they are already taking tizanidine.
- that ciprofloxacin extended-release tablets may increase the effects of theophylline and caffeine. There is a possibility of caffeine accumulation when products containing caffeine are consumed while taking quinolones.
- that convulsions have been reported in patients receiving quinolones, including ciprofloxacin, and to notify their physician before taking ciprofloxacin extended-release tablets if there is a history of this condition.
- that diarrhea is a common problem caused by antibiotics which usually ends when the antibiotic is discontinued. Sometimes after starting treatment with antibiotics, patients can develop watery and bloody stools (with or without stomach cramps and fever) even as late as two or more months after having taken the last dose of the antibiotic. If this occurs, patients should contact their physician as soon as possible.

Drug Interactions

In a pharmacokinetic study, systemic exposure of tizanidine (4 mg single dose) was significantly increased (Cmax 7-fold, AUC 10-fold) when the drug was given concomitantly with ciprofloxacin (500 mg bid for 3 days). The hypotensive and sedative effects of tizanidine were also potentiated. Concomitant administration of tizanidine and ciprofloxacin is contraindicated.

As with some other quinolones, concurrent administration of ciprofloxacin with theophylline may lead to elevated serum concentrations of theophylline and prolongation of its elimination half-life. This may result in increased risk of theophylline-related adverse reactions. (See WARNINGS.) If concomitant use cannot be avoided, serum levels of theophylline should be monitored and dosage adjustments made as appropriate.

Some quinolones, including ciprofloxacin, have also been shown to interfere with the metabolism of caffeine. This may lead to reduced clearance of caffeine and a prolongation of its serum half-life.

Concurrent administration of a quinolone, including ciprofloxacin, with multivalent cation-containing products such as magnesium/aluminum antacids, sucralfate, VIDEX® (didanosine) chewable/buffered tablets or pediatric powder, other highly buffered drugs, or products containing calcium, iron, or zinc may substantially interfere with the absorption of the quinolone, resulting in serum and urine levels considerably lower than desired. Ciprofloxacin extended-release tablets should be administered at least 2 hours before or 6 hours after antacids containing magnesium or aluminum, as well as sucralfate, VIDEX® (didanosine) chewable/buffered tablets or pediatric powder, other highly buffered drugs, metal cations such as iron, and multivitamin preparations with zinc. (See CLINICAL PHARMACOLOGY, Drug-drug Interactions, PRECAUTIONS, Information for Patients, and DOSAGE AND ADMINISTRATION.)

Histamine H2-receptor antagonists appear to have no significant effect on the bioavailability of ciprofloxacin.

Absorption of the ciprofloxacin extended-release tablet was slightly diminished (20%) when given concomitantly with omeprazole. (See CLINICAL PHARMACOLOGY, Drug-drug Interactions.)

Altered serum levels of phenytoin (increased and decreased) have been reported in patients receiving concomitant ciprofloxacin.

The concomitant administration of ciprofloxacin with the sulfonylurea glyburide has, on rare occasions, resulted in severe hypoglycemia.

Some quinolones, including ciprofloxacin, have been associated with transient elevations in serum creatinine in patients receiving cyclosporine concomitantly.

Quinolones, including ciprofloxacin, have been reported to enhance the effects of the oral anticoagulant warfarin or its derivatives. When these products are administered concomitantly, prothrombin time or other suitable coagulation tests should be closely monitored.

Probenecid interferes with renal tubular secretion of ciprofloxacin and produces an increase in the level of ciprofloxacin in the serum. This should be considered if patients are receiving both drugs concomitantly.

Renal tubular transport of methotrexate may be inhibited by concomitant administration of ciprofloxacin potentially leading to increased plasma levels of methotrexate. This might increase the risk of methotrexate associated toxic reactions. Therefore, patients under methotrexate therapy should be carefully monitored when concomitant ciprofloxacin therapy is indicated.

Metoclopramide significantly accelerates the absorption of oral ciprofloxacin resulting in a shorter time to reach maximum plasma concentrations. No significant effect was observed on the bioavailability of ciprofloxacin.

Non-steroidal anti-inflammatory drugs (but not acetyl salicylic acid) in combination of very high doses of quinolones have been shown to provoke convulsions in pre-clinical studies.

Carcinogenesis, Mutagenesis, Impairment of Fertility

Eight in vitro mutagenicity tests have been conducted with ciprofloxacin, and the test results are listed below:
Salmonella/Microsome Test (Negative)
E. coli DNA Repair Assay (Negative)
Mouse Lymphoma Cell Forward Mutation Assay (Positive)
Chinese Hamster V79 Cell HGPRT Test (Negative)
Syrian Hamster Embryo Cell Transformation Assay (Negative)
Saccharomyces cerevisiae Point Mutation Assay (Negative)
Saccharomyces cerevisiae Mitotic Crossover and Gene Conversion Assay (Negative)
Rat Hepatocyte DNA Repair Assay (Positive)

Thus, 2 of the 8 tests were positive, but results of the following 3 in vivo test systems gave negative results:
Rat Hepatocyte DNA Repair Assay
Micronucleus Test (Mice)
Dominant Lethal Test (Mice)

Ciprofloxacin was not carcinogenic or tumorigenic in 2-year carcinogenicity studies with rats and mice at daily oral dose levels of 250 and 750 mg/kg, respectively (approximately 2 and 3 -fold greater than the 1000 mg daily human dose based upon body surface area).

Results from photo co-carcinogenicity testing indicate that ciprofloxacin does not reduce the time to appearance of UV-induced skin tumors as compared to vehicle control. Hairless (Skh-1) mice were exposed to UVA light for 3.5 hours five times every two weeks for up to 78 weeks while concurrently being administered ciprofloxacin. The time to development of the first skin tumors was 50 weeks in mice treated concomitantly with UVA and ciprofloxacin (mouse dose approximately equal to the maximum recommended daily human dose of 1000 mg based upon mg/m^2), as opposed to 34 weeks when animals were treated with both UVA and vehicle. The times to development of skin tumors ranged from 16-32 weeks in mice treated concomitantly with UVA and other quinolones.

In this model, mice treated with ciprofloxacin alone did not develop skin or systemic tumors. There are no data from similar models using pigmented mice and/or fully haired mice. The clinical significance of these findings to humans is unknown.

Fertility studies performed in rats at oral doses of ciprofloxacin up to 100 mg/kg (1.0 times the highest recommended daily human dose of 1000 mg based upon body surface area) revealed no evidence of impairment.

Pregnancy

Teratogenic Effects

Pregnancy Category C

There are no adequate and well-controlled studies in pregnant women. An expert review of published data on experiences with ciprofloxacin use during pregnancy by TERIS - the Teratogen Information System – concluded that therapeutic doses during pregnancy are unlikely to pose a substantial teratogenic risk (quantity and quality of data=fair), but the data are insufficient to state there is no risk.

A controlled prospective observational study followed 200 women exposed to fluoroquinolones (52.5% exposed to ciprofloxacin and 68% first trimester exposures) during gestation. In utero exposure to fluoroquinolones during embryogenesis was not associated with increased risk of major malformations. The reported rates of major congenital malformations were 2.2% for the fluoroquinolone group and 2.6% for the control group (background incidence of major malformations is 1-5%). Rates of spontaneous abortions, prematurity and low birth weight did not differ between the groups and there were no clinically significant musculoskeletal dysfunctions up to one year of age in the ciprofloxacin exposed children.

Another prospective follow-up study reported on 549 pregnancies with fluoroquinolone exposure (93% first trimester exposures).There were 70 ciprofloxacin exposures, all within the first trimester. The malformation rates among live-born babies exposed to ciprofloxacin and to fluoroquinolones overall were both within background incidence ranges. No specific patterns of congenital abnormalities were found. The study did not reveal any clear adverse reactions due to in utero exposure to ciprofloxacin.

No differences in the rates of prematurity, spontaneous abortions, or birth weight were seen in women exposed to ciprofloxacin during pregnancy. However, these small postmarketing epidemiology studies, of which most experience is from short term, first trimester exposure, are insufficient to evaluate the risk for the less common defects or to permit reliable and definitive conclusions regarding the safety of ciprofloxacin in pregnant women and their developing fetuses. Ciprofloxacin should not be used during pregnancy unless potential benefit justifies the potential risk to both fetus and mother (see WARNINGS).

Reproduction studies have been performed in rats and mice using oral doses up to 100 mg/kg (0.7 and 0.4 times the maximum daily human dose of 1000 mg based upon body surface area, respectively) and have revealed no evidence of harm to the fetus due to ciprofloxacin. In rabbits, ciprofloxacin (30 and 100 mg/kg orally) produced gastrointestinal disturbances resulting in maternal weight loss and an increased incidence of abortion, but no teratogenicity was observed at either dose. After intravenous administration of doses up to 20 mg/kg, no maternal toxicity was produced in the rabbit, and no embryotoxicity or teratogenicity was observed.

Nursing Mothers

Ciprofloxacin is excreted in human milk. The amount of ciprofloxacin absorbed by the nursing infant is unknown. Because of the potential for serious adverse reactions in infants nursing from mothers taking ciprofloxacin, a decision should be made whether to discontinue nursing or to discontinue the drug, taking into account the importance of the drug to the mother.

Pediatric Use

Safety and effectiveness of ciprofloxacin extended-release tablets in pediatric patients and adolescents less than 18 years of age have not been established. Ciprofloxacin causes arthropathy in juvenile animals. (See WARNINGS.)

Geriatric Use

Geriatric patients are at increased risk for developing severe tendon disorders including tendon rupture when being treated with a fluoroquinolone such as ciprofloxacin extended-release tablets. This risk is further increased in patients receiving concomitant corticosteroid therapy. Tendinitis or tendon rupture can involves the Achilles, hand, shoulder, or other tendon sites and can occur during or after completion of therapy; cases occurring up to several months after fluoroquinolone treatment have been reported. Caution should be used when prescribing ciprofloxacin extended-release tablets to elderly patients especially those on corticosteroids. Patients should be informed of this potential side effect and advised to discontinue ciprofloxacin extended-release tablets and contact their healthcare provider if any symptoms of tendinitis or tendon rupture occur (See Boxed Warning, WARNINGS, and ADVERSEREACTIONS/Post-Marketing Adverse Event Reports).

In a large, prospective, randomized ciprofloxacin extended-release tablets clinical trial in urinary tract infections, 49% (509/1035) of the patients were 65 and over, while 30% (308/1035) were 75 and over. No overall differences in safety or effectiveness were observed between these subjects and younger subjects, and clinical experience with other formulations of ciprofloxacin has not identified differences in responses between the elderly and younger patients, but greater sensitivity of some older individuals cannot be ruled out. Ciprofloxacin is known to be substantially excreted by the kidney, and the risk of adverse reactions may be greater in patients with impaired renal function. No alteration of dosage is necessary for patients greater than 65 years of age with normal renal function. However, since some older individuals experience reduced renal function by virtue of their advanced age, care should be taken in dose selection for elderly patients, and renal function monitoring may be useful in these patients. (See CLINICAL PHARMACOLOGY and DOSAGE AND ADMINISTRATION.)

In general, elderly patients may be more susceptible to drug-associated effects on the QT interval. Therefore, precaution should be taken when using ciprofloxacin extended-release tablets with concomitant drugs that can result in prolongation of the QT interval (e.g., class IA or class III antiarrhythmics) or in patients with risk factors for torsade de pointes (e.g., known QT prolongation, uncorrected hypokalemia).

ADVERSE REACTIONS

Clinical trials in patients with urinary tract infections enrolled 961 patients treated with 500 mg or 1000 mg ciprofloxacin extended-release tablets. Most adverse events reported were described as mild to moderate in severity and required no treatment. The overall incidence, type and distribution of adverse events were similar in patients receiving both 500 mg and 1000 mg of ciprofloxacin extended-release tablets. Because clinical trials are conducted under widely varying conditions, adverse reaction rates observed in clinical trials of a drug cannot be directly compared to rates observed in clinical trials of another drug and may not reflect the rates observed in practice. The adverse reaction information from clinical studies does, however, provide a basis for identifying the adverse events that appear to be related to drug use and for approximating rates.

In the clinical trial of uncomplicated urinary tract infection, ciprofloxacin extended-release tablets (500 mg once daily) in 444 patients was compared to ciprofloxacin immediate-release tablets (250 mg twice daily) in 447 patients for 3 days. Discontinuations due to adverse reactions thought to be drug-related occurred in 0.2% (1/444) of patients in the ciprofloxacin extended-release tablets arm and in 0% (0/447) of patients in the control arm.

In the clinical trial of complicated urinary tract infection and acute uncomplicated pyelonephritis, ciprofloxacin extended-release tablets (1000 mg once daily) in 517 patients was compared to ciprofloxacin immediate-release tablets (500 mg twice daily) in 518 patients for 7 to 14 days. Discontinuations due to adverse reactions thought to be drug-related occurred in 3.1% (16/517) of patients in the ciprofloxacin extended-release tablets arm and in 2.3% (12/518) of patients in the control arm. The most common reasons for discontinuation in the ciprofloxacin extended-release tablets arm were nausea/vomiting (4 patients) and dizziness (3 patients). In the control arm the most common reason for discontinuation was nausea/vomiting (3 patients).

In these clinical trials, the following events occurred in ≥ 2% of all ciprofloxacin extended-release tablets patients, regardless of drug relationship: nausea (4%), headache (3%), dizziness (2%), diarrhea (2%), vomiting (2%) and vaginal moniliasis (2%).

Adverse events, judged by investigators to be at least possibly drug-related, occurring in greater than or equal to 1% of all ciprofloxacin extended-release tablets treated patients were: nausea (3%), diarrhea (2%), headache (1%), dyspepsia (1%), dizziness (1%), and vaginal moniliasis (1%). Vomiting (1%) occurred in the 1000 mg group.

Additional uncommon events, judged by investigators to be at least possibly drug-related, that occurred in less than 1% of ciprofloxacin extended-release tablets treated patients were:

Body As a Whole: abdominal pain, asthenia, malaise, photosensitivity reaction
Cardiovascular: bradycardia, migraine, syncope
Digestive: anorexia, constipation, dry mouth, flatulence, liver function tests abnormal, thirst
Hemic/Lymphatic: prothrombin decrease
Central Nervous System: abnormal dreams, depersonalization, depression, hypertonia, incoordination, insomnia, somnolence, tremor, vertigo
Metabolic: hyperglycemia
Skin/Hypersensivity: dry skin, maculopapular rash, photosensitivity/phototoxicity reactions, pruritus, rash, skin disorder, urticaria, vesiculobullous rash
Special Senses: diplopia, taste perversion
Urogenital: dysmenorrhea, hematuria, kidney function abnormal, vaginitis

Post-Marketing Adverse Event Reports: The following adverse events have been reported from worldwide marketing experience with fluoroquinolones, including ciprofloxacin. Because these reactions have been reported voluntarily from a population of uncertain size, it is not always possible to reliably estimate their frequency or a causal relationship to drug exposure. The events in alphabetical order are:

abnormal gait, achiness, acidosis, agitation, agranulocytosis, allergic reactions (ranging from urticaria to anaphylactic reactions and including life-threatening anaphylactic shock), amylase increase, anemia, angina pectoris, angioedema, anosmia, anxiety, arrhythmia, arthralgia, ataxia, atrial flutter, bleeding diathesis, blurred vision, bronchospasm, C. difficile associated diarrhea, candidiasis (cutaneous, oral), candiduria, cardiac murmur, cardiopulmonary arrest, cardiovascular collapse, cerebral thrombosis, chills, cholestatic jaundice, chromatopsia, confusion, convulsion, delirium, drowsiness, dysphagia, dysphasia, dyspnea, edema (conjunctivae, face, hands, laryngeal, lips, lower extremities, neck, pulmonary), epistaxis, erythema multiforme, erythema nodosum, exfoliative dermatitis, fever, fixed eruptions, flushing, gastrointestinal bleeding, gout (flare up), grand mal convulsion, gynecomastia, hallucinations, hearing loss, hemolytic anemia, hemoptysis, hemorrhagic cystitis, hepatic failure (including fatal cases), hepatic necrosis, hepatitis, hiccup, hyperesthesia, hyperpigmentation, hypertension, hypertonia, hypesthesia, hypotension, ileus, interstitial nephritis, intestinal perforation, jaundice, joint stiffness, lethargy, lightheadedness, lipase increase, lymphadenopathy, manic reaction, marrow depression, migraine, moniliasis (oral, gastrointestinal, vaginal), myalgia, myasthenia, exacerbation of myasthenia gravis, myocardial infarction, myoclonus, nephritis, nightmares, nystagmus, oral ulceration, pain (arm, back, breast, chest, epigastric, eye, extremities, foot, jaw, neck, oral mucosa), palpitation, pancreatitis, pancytopenia, paranoia, paresthesia, peripheral neuropathy, perspiration (increased), petechia, phlebitis, phobia, photosensitivity/phototoxicity reaction, pleural effusion, polyuria, postural hypotension, prothrombin time prolongation, pseudomembranous colitis (the onset of symptoms may occur during or after antimicrobial treatment), pulmonary embolism, purpura, renal calculi, renal failure, respiratory arrest, respiratory distress, restlessness, serum sickness-like reaction, Stevens-Johnson syndrome, sweating, tachycardia, taste loss, tendinitis, tendon rupture, tinnitus, torsade de pointes, toxic epidermal necrolysis (Lyell's syndrome), toxic psychosis, twitching, unresponsiveness, urethral bleeding, urinary retention, urination (frequent), vaginal pruritus, vasculitis, ventricular ectopy, vesicles, visual acuity (decreased), visual disturbances (flashing lights, change in color perception, overbrightness of lights).

Laboratory Changes

The following adverse laboratory changes, in alphabetical order, regardless of incidence or relationship to drug, have been reported in patients given ciprofloxacin (includes all formulations, all dosages, all drug-therapy durations, and all indications):

Decreases in blood glucose, BUN, hematocrit, hemoglobin, leukocyte counts, platelet counts, prothrombin time, serum albumin, serum potassium, total serum protein, uric acid.

Increases in alkaline phosphatase, ALT (SGPT), AST (SGOT), atypical lymphocyte counts, blood glucose, blood monocytes, BUN, cholesterol, eosinophil counts, LDH, platelet counts, prothrombin time, sedimentation rate, serum amylase, serum bilirubin, serum calcium, serum cholesterol, serum creatine phosphokinase, serum creatinine, serum gamma-glutamyl transpeptidase (GGT), serum potassium, serum theophylline (in patients receiving theophylline concomitantly), serum triglycerides, uric acid.

Others: albuminuria, change in serum phenytoin, crystalluria, cylindruria, immature WBCs, leukocytosis, methemoglobinemia, pancytopenia.

OVERDOSAGE

In the event of acute excessive overdosage, reversible renal toxicity has been reported in some cases. The stomach should be emptied by inducing vomiting or by gastric lavage. The patient should be carefully observed and given supportive treatment, including monitoring of renal function and administration of magnesium or calcium containing antacids which can reduce the absorption of ciprofloxacin. Adequate hydration must be maintained. Only a small amount of ciprofloxacin (< 10%) is removed from the body after hemodialysis or peritoneal dialysis.

In mice, rats, rabbits and dogs, significant toxicity including tonic/clonic convulsions was observed at intravenous doses of ciprofloxacin between 125 and 300 mg/kg.

Single doses of ciprofloxacin were relatively non-toxic via the oral route of administration in mice, rats, and dogs. No deaths occurred within a 14-day post treatment observation period at the highest oral doses tested; up to 5000 mg/kg in either rodent species, or up to 2500 mg/kg in the dog. Clinical signs observed included hypoactivity and cyanosis in both rodent species and severe vomiting in dogs. In rabbits, significant mortality was seen at doses of ciprofloxacin > 2500 mg/kg. Mortality was delayed in these animals, occurring 10-14 days after dosing.

DOSAGE AND ADMINISTRATION

Ciprofloxacin extended-release tablets and ciprofloxacin immediate-release tablets are not interchangeable. Ciprofloxacin extended-release tablets should be administered orally once daily as described in the following Dosage Guidelines table:

DOSAGE GUIDELINES
Indication | Unit Dose | Frequency | Usual Duration
Uncomplicated Urinary Tract Infection (Acute Cystitis) | 500 mg | Q24h | 3 Days
Complicated Urinary Tract Infection | 1000 mg | Q24h | 7-14 Days
Acute Uncomplicated Pyelonephritis | 1000 mg | Q24h | 7-14 Days

Patients whose therapy is started with ciprofloxacin I.V. for urinary tract infections may be switched to ciprofloxacin extended-release tablets when clinically indicated at the discretion of the physician.

Ciprofloxacin extended-release tablets should be administered at least 2 hours before or 6 hours after antacids containing magnesium or aluminum, as well as sucralfate, VIDEX® (didanosine) chewable/buffered tablets or pediatric powder, other highly buffered drugs, metal cations such as iron, and multivitamin preparations with zinc. Although ciprofloxacin extended-release tablets may be taken with meals that include milk, concomitant administration with dairy products alone, or with calcium-fortified products should be avoided, since decreased absorption is possible. A 2-hour window between substantial calcium intake (> 800 mg) and dosing with ciprofloxacin extended-release tablets are recommended. Ciprofloxacin extended-release tablets should be swallowed whole. DO NOT SPLIT, CRUSH, OR CHEW THE TABLET. (See CLINICAL PHARMACOLOGY, Drug-drug Interactions, PRECAUTIONS, Drug Interactions and Information for Patients.)

Impaired Renal Function

Ciprofloxacin is eliminated primarily by renal excretion; however, the drug is also metabolized and partially cleared through the biliary system of the liver and through the intestine. These alternate pathways of drug elimination appear to compensate for the reduced renal excretion in patients with renal impairment. No dosage adjustment is required for patients with uncomplicated urinary tract infections receiving 500 mg ciprofloxacin extended-release tablets. In patients with complicated urinary tract infections and acute uncomplicated pyelonephritis, who have a creatinine clearance of < 30 mL/min, the dose of ciprofloxacin extended-release tablets should be reduced from 1000 mg to 500 mg daily. For patients on hemodialysis or peritoneal dialysis, administer ciprofloxacin extended-release tablets after the dialysis procedure is completed. (See CLINICAL PHARMACOLOGY, Special Populations, and PRECAUTIONS, Geriatric Use.)

Impaired Hepatic Function

No dosage adjustment is required with ciprofloxacin extended-release tablets in patients with stable chronic cirrhosis. The kinetics of ciprofloxacin in patients with acute hepatic insufficiency, however, have not been fully elucidated. (See CLINICAL PHARMACOLOGY, Special Populations.)

HOW SUPPLIED

Ciprofloxacin extended-release tablets, 500 mg are white to off-white, film coated, oblong shaped, biconvex tablets, embossed with ‘RDY’ on one side and ‘422’ on other side. They are supplied in bottles of 30's, 100's, 500's and unit-dose package of 100 (10×10).

Bottles of 30 | NDC 55111-422-30
Bottles of 100 | NDC 55111-422-01
Bottles of 500 | NDC 55111-422-05
Unit-dose package of 100 (10×10) | NDC 55111-422-78

Ciprofloxacin extended-release tablets, 1000 mg are white to off-white, film coated, oblong shaped, biconvex tablets, embossed with ‘RDY’on one side and ‘423’ on other side. They are supplied in bottles of 30's, 100's, 500's and unit-dose packages of 100 (10×10).

Bottles of 30 | NDC 55111-423-30
Bottles of 100 | NDC 55111-423-01
Bottles of 500 | NDC 55111-423-05
Unit-dose package of 100 (10×10) | NDC 55111-423-78

STORAGE AND HANDLING

Store at 20°-25°C (68°-77°F); excursions permitted to 15°-30°C (59°-86°F) [see USP Controlled Room Temperature].

ANIMAL PHARMACOLOGY

Ciprofloxacin and other quinolones have been shown to cause arthropathy in immature animals of most species tested. (See WARNINGS.) Damage of weight bearing joints was observed in juvenile dogs and rats. In young beagles, 100 mg/kg ciprofloxacin, given daily for 4 weeks, caused degenerative articular changes of the knee joint. At 30 mg/kg, the effect on the joint was minimal. In a subsequent study in beagles, removal of weight bearing from the joint reduced the lesions but did not totally prevent them.

Crystalluria, sometimes associated with secondary nephropathy, occurs in laboratory animals dosed with ciprofloxacin. This is primarily related to the reduced solubility of ciprofloxacin under alkaline conditions, which predominate in the urine of test animals; in man, crystalluria is rare since human urine is typically acidic. In rhesus monkeys, crystalluria without nephropathy has been noted after single oral doses as low as 5 mg/kg. After 6 months of intravenous dosing at 10 mg/kg/day, no nephropathological changes were noted; however, nephropathy was observed after dosing at 20 mg/kg/day for the same duration.

In mice, concomitant administration of nonsteroidal anti-inflammatory drugs such as phenylbutazone and indomethacin with quinolones has been reported to enhance the CNS stimulatory effect of quinolones.

Ocular toxicity seen with some related drugs has not been observed in ciprofloxacin-treated animals.

CLINICAL STUDIES

Uncomplicated Urinary Tract Infections (acute cystitis)

Ciprofloxacin extended-release tablets was evaluated for the treatment of uncomplicated urinary tract infections (acute cystitis) in a randomized, double-blind, controlled clinical trial conducted in the US. This study compared ciprofloxacin extended-release tablets (500 mg once daily for three days) with ciprofloxacin immediate-release tablets (ciprofloxacin 250 mg BID for three days). Of the 905 patients enrolled, 452 were randomly assigned to the ciprofloxacin extended-release tablets treatment group and 453 were randomly assigned to the control group. The primary efficacy variable was bacteriologic eradication of the baseline organism(s) with no new infection or superinfection at test-of-cure (Day 4 -11 Post-therapy).

The bacteriologic eradication and clinical success rates were similar between ciprofloxacin extended-release tablets and the control group. The eradication and clinical success rates and their corresponding 95% confidence intervals for the differences between rates (ciprofloxacin extended-release tablets minus control group) are given in the following table:

 | Ciprofloxacin extended-release tablets 500 mg QD × 3 Days | Ciprofloxacin tablets 250 mg BID × 3 Days
Randomized Patients | 452 | 453
Per Protocol Patients [The presence of a pathogen at a level of ≥ 10^5 CFU/mL was required for microbiological evaluability criteria, except for S. saprophyticus (≥ 10^4 CFU/mL).] | 199 | 223
Bacteriologic Eradication at TOC (n/N) [n/N = patients with baseline organism(s) eradicated and no new infections or superinfections/ total number of patients] | 188/199 (94.5%) | 209/223 (93.7%)
 | CI [-3.5%, 5.1%]
Bacteriologic Eradication (by organism) at TOC (n/N) [n/N = patients with specified baseline organism eradicated/patients with specified baseline organism]
E. coli | 156/160 (97.5%) | 176/181 (97.2%)
E. faecalis | 10/11 (90.9%) | 17/21 (81.0%)
P. mirabilis | 11/12 (91.7%) | 7/7 (100%)
S. saprophyticus | 6/7 (85.7%) | 9/9 (100%)
Clinical Response at TOC (n/N) [n/N = patients with clinical success /total number of patients] | 189/199 (95.0%) | 204/223 (91.5%)
 | CI [-1.1%, 8.1%]

Complicated Urinary Tract Infections and Acute Uncomplicated Pyelonephritis

Ciprofloxacin extended-release tablets was evaluated for the treatment of complicated urinary tract infections (cUTI) and acute uncomplicated pyelonephritis (AUP) in a randomized, double-blind, controlled clinical trial conducted in the US and Canada. The study enrolled 1,042 patients (521 patients per treatment arm) and compared ciprofloxacin extended-release tablets (1000 mg once daily for 7 to 14 days) with immediate-release ciprofloxacin (500 mg BID for 7 to 14 days). The primary efficacy endpoint for this trial was bacteriologic eradication of the baseline organism(s) with no new infection or superinfection at 5 to 11 days post-therapy (test-of-cure or TOC) for the Per Protocol and Modified Intent-To-Treat (MITT) populations.

The Per Protocol population was defined as patients with a diagnosis of cUTI or AUP, a causative organism(s) at baseline present at ≥ 10^5 CFU/mL, no inclusion criteria violation, a valid test-of-cure urine culture within the TOC window, an organism susceptible to study drug, no premature discontinuation or loss to follow-up, and compliance with the dosage regimen (among other criteria).

More patients in the ciprofloxacin extended-release tablets arm than in the control arm were excluded from the Per Protocol population and this should be considered in the interpretation of the study results. Reasons for exclusion with the greatest discrepancy between the two arms were no valid test-of-cure urine culture, an organism resistant to the study drug, and premature discontinuation due to adverse events.

An analysis of all patients with a causative organism(s) isolated at baseline and who received study medication, defined as the MITT population, included 342 patients in the ciprofloxacin extended-release tablets arm and 324 patients in the control arm. Patients with missing responses were counted as failures in this analysis. In the MITT analysis of cUTI patients, bacteriologic eradication was 160/271 (59.0%) versus 156/248 (62.9%) in ciprofloxacin extended-release tablets and control arm, respectively [97.5% CI [confidence interval of the difference in rates (ciprofloxacin extended-release tablets minus control).] (-13.5%, 5.7%)]. Clinical cure was 184/271 (67.9%) for ciprofloxacin extended-release tablets and 182/248 (73.4%) for control arm, respectively [97.5% CI (-14.4%, 3.5%)]. Bacterial eradication in the MITT analysis of patients with AUP at TOC was 47/71 (66.2%) and 58/76 (76.3%) for ciprofloxacin extended-release tablets and control arm, respectively [97.5% CI (-26.8%, 6.5%)]. Clinical cure at TOC was 50/71 (70.4%) for ciprofloxacin extended-release tablets and 58/76 (76.3%) for the control arm [97.5% CI (-22.0%, 10.4%)].

In the Per Protocol population, the differences between ciprofloxacin extended-release tablets and the control arm in bacteriologic eradication rates at the TOC visit were not consistent between AUP and cUTI patients. The bacteriologic eradication rate for cUTI patients was higher in the ciprofloxacin extended-release tablets arm than in the control arm. For AUP patients, the bacteriologic eradication rate was lower in the ciprofloxacin extended-release tablets arm than in the control arm. This inconsistency was not observed between the two treatment groups for clinical cure rates. Clinical cure rates were 96.1% (198/206) and 92.1% (211/229) for ciprofloxacin extended-release tablets and the control arm, respectively.

The bacterial eradication and clinical cure rates by infection type for ciprofloxacin extended-release tablets and the control arm at the TOC visit and their corresponding 97.5% confidence intervals for the differences between rates (ciprofloxacin extended-release tablets minus control arm) are given below for the Per Protocol population analysis:

 | CIPROFLOXACIN EXTENDED-RELEASE TABLETS 1000 mg QD | CIPROFLOXACIN TABLETS 500 mg BID
Randomized Patients | 521 | 521
Per Protocol Patients [Patients excluded from the Per Protocol population were primarily those with no causative organism(s) at baseline or no organism present at ≥ 10^5 CFU/mL at baseline, inclusion criteria violation, no valid test-of-cure urine culture within the TOC window, an organism resistant to study drug, premature discontinuation due to an adverse event, lost to follow-up, or non-compliance with dosage regimen (among other criteria).] | 206 | 229
cUTI Patients
Bacteriologic Eradication at TOC (n/N) [n/N = patients with baseline organism(s) eradicated and no new infections or superinfections/total number of patients] | 148/166 (89.2%) | 144/177 (81.4%)
 | CI [-0.7%, 16.3%]
Bacteriologic Eradication (by organism) at TOC (n/N) [n/N = patients with specified baseline organism eradicated/patients with specified baseline organism]
E. coli | 91/94 (96.8%) | 90/92 (97.8%)
K. pneumoniae | 20/21 (95.2%) | 19/23 (82.6%)
E. faecalis | 17/17 (100%) | 14/21 (66.7%)
P. mirabilis | 11/12 (91.6%) | 10/10 (100%)
P. aeruginosa | 3/3 (100%) | 3/3 (100%)
Clinical Cure at TOC (n/N) [n/N = patients with clinical success /total number of patients] | 159/166 (95.8%) | 161/177 (91.0%)
 | CI [-1.1%, 10.8%]
AUP Patients
Bacteriologic Eradication at TOC (n/N) | 35/40 (87.5%) | 51/52 (98.1%)
 | CI [-34.8%, 6.2%]
Bacteriologic Eradication of E. coli at TOC (n/N) | 35/36 (97.2%) | 41/41 (100%)
Clinical Cure at TOC (n/N) | 39/40 (97.5%) | 50/52 (96.2%)
 | CI [-15.3%, 21.1%]

Of the 166 cUTI patients treated with ciprofloxacin extended-release tablets, 148 (89%) had the causative organism(s) eradicated, 8 (5%) had persistence, 5 (3%) patients developed superinfections and 5 (3%) developed new infections. Of the 177 cUTI patients treated in the control arm, 144 (81%) had the causative organism(s) eradicated, 16 (9%) patients had persistence, 3 (2%) developed superinfections and 14 (8%) developed new infections. Of the 40 patients with AUP treated with ciprofloxacin extended-release tablets, 35 (87.5%) had the causative organism(s) eradicated, 2 (5%) patients had persistence and 3 (7.5%) developed new infections. Of the 5 ciprofloxacin extended-release tablets AUP patients without eradication at TOC, 4 were considered clinical cures and did not receive alternative antibiotic therapy. Of the 52 patients with AUP treated in the control arm, 51 (98%) had the causative organism(s) eradicated. One patient (2%) had persistence.

References

1. Clinical and Laboratory Standards Institute. Methods for Dilution Antimicrobial Susceptibility Tests for Bacteria That Grow Aerobically; Approved Standard – Eighth Edition. CLSI Document M7-A8, Vol. 29, No. 2, CLSI, Wayne, PA, January, 2009.
2. Clinical and Laboratory Standards Institute. Performance Standards for Antimicrobial Disk Susceptibility Tests; Approved Standard – Tenth Edition. CLSI Document M2-A10, Vol. 29, No. 1, CLSI, Wayne, PA, January, 2009.

Rx Only

Manufactured by:
Dr. Reddy's Laboratories Limited
Bachepalli – 502 325 INDIA

Revised:0811

MEDICATION GUIDE

CIPROFLOXACIN TABLETS, USP

CIPROFLOXACIN EXTENDED-RELEASE TABLETS

READ THE MEDICATION GUIDE THAT COMES WITH CIPROFLOXACIN TABLETS BEFORE YOU START TAKING IT AND EACH TIME YOU GET A REFILL. THERE MAY BE NEW INFORMATION. THIS MEDICATION GUIDE DOES NOT TAKE THE PLACE OF TALKING TO YOUR HEALTHCARE PROVIDER ABOUT YOUR MEDICAL CONDITION OR YOUR TREATMENT.

What is the most important information I should know about ciprofloxacin tablets?

CIPROFLOXACIN BELONGS TO A CLASS OF ANTIBIOTICS CALLED FLUOROQUINOLONES. CIPROFLOXACIN TABLETS CAN CAUSE SIDE EFFECTS THAT MAY BE SERIOUS OR EVEN CAUSE DEATH. IF YOU GET ANY OF THE FOLLOWING SERIOUS SIDE EFFECTS, GET MEDICAL HELP RIGHT AWAY. TALK WITH YOUR HEALTHCARE PROVIDER ABOUT WHETHER YOU SHOULD CONTINUE TO TAKE CIPROFLOXACIN TABLETS.

1. Tendon rupture or swelling of the tendon (tendinitis)

- Tendon problems can happen in people of all ages who take ciprofloxacin tablets.
  - Tendons are tough cords of tissue that connect muscles to bones. Symptoms of tendon problems may include:
  - Pain, swelling, tears, and inflammation of tendons including the back of the ankle (Achilles), shoulder, hand, or other tendon sites.
- The risk of getting tendon problems while you take ciprofloxacin tablets is higher if you:
  - are over 60 years of age
  - are taking steroids (corticosteroids)
  - have had a kidney, heart, or lung transplant.

- Tendon problems can happen in people who do not have the above risk factors when they take ciprofloxacin tablets. Other reasons that can increase your risk of tendon problems can include:
  - physical activity or exercise
  - kidney failure
  - tendon problems in the past, such as in people with rheumatoid arthritis (RA)

- Call your healthcare provider right away at the first sign of tendon pain, swelling or inflammation. Stop taking ciprofloxacin tablets until tendinitis or tendon rupture has been ruled out by your healthcare provider. Avoid exercise and using the affected area. The most common area of pain and swelling is the Achilles tendon at the back of your ankle. This can also happen with other tendons.
- Talk to your healthcare provider about the risk of tendon rupture with continued use of ciprofloxacin tablets. You may need a different antibiotic that is not a fluoroquinolone to treat your infection.
- Tendon rupture can happen while you are taking or after you have finished taking ciprofloxacin tablets. Tendon ruptures have happened up to several months after patients have finished taking their fluoroquinolone.
- Get medical help right away if you get any of the following signs or symptoms of a tendon rupture:
  - hear or feel a snap or pop in a tendon area
  - bruising right after an injury in a tendon area
  - unable to move the affected area or bear weight

2. WORSENING OF MYASTHENIA GRAVIS (A DISEASE WHICH CAUSES MUSCLE WEAKNESS).

FLUOROQUINOLONES LIKE CIPROFLOXACIN MAY CAUSE WORSENING OF MYASTHENIA GRAVIS SYMPTOMS, INCLUDING MUSCLE WEAKNESS AND BREATHING PROBLEMS. CALL YOUR HEALTHCARE PROVIDER RIGHT AWAY IF YOU HAVE ANY WORSENING MUSCLE WEAKNESS OR BREATHING PROBLEMS.

SEE THE SECTION “WHAT ARE THE POSSIBLE SIDE EFFECTS OF CIPROFLOXACIN TABLETS?” FOR MORE INFORMATION ABOUT SIDE EFFECTS.

What are ciprofloxacin tablets?

Ciprofloxacin tablet is a fluoroquinolone antibiotic medicine used to treat certain infections caused by certain germs called bacteria.

Children less than 18 years of age have a higher chance of getting bone, joint, or tendon (musculoskeletal) problems such as pain or swelling while taking ciprofloxacin tablets.

Ciprofloxacin tablets should not be used as the first choice of antibiotic medicine in children under 18 years of age. Ciprofloxacin tablets should not be used in children under 18 years old, except to treat specific serious infections, such as complicated urinary tract infections and to prevent anthrax disease after breathing the anthrax bacteria germ (inhalational exposure). It is not known if ciprofloxacin extended-release tablets are safe and works in children under 18 years of age.

SOMETIMES INFECTIONS ARE CAUSED BY VIRUSES RATHER THAN BY BACTERIA. EXAMPLES INCLUDE VIRAL INFECTIONS IN THE SINUSES AND LUNGS, SUCH AS THE COMMON COLD OR FLU. ANTIBIOTICS, INCLUDING CIPROFLOXACIN TABLETS, DO NOT KILL VIRUSES.

CALL YOUR HEALTHCARE PROVIDER IF YOU THINK YOUR CONDITION IS NOT GETTING BETTER WHILE YOU ARE TAKING CIPROFLOXACIN TABLETS.

Who should not take ciprofloxacin tablets?

DO NOT TAKE CIPROFLOXACIN TABLETS IF YOU:

- HAVE EVER HAD A SEVERE ALLERGIC REACTION TO AN ANTIBIOTIC KNOWN AS A FLUOROQUINOLONE, OR ARE ALLERGIC TO ANY OF THE INGREDIENTS IN CIPROFLOXACIN TABLETS. ASK YOUR HEALTHCARE PROVIDER IF YOU ARE NOT SURE. SEE THE LIST OF INGREDIENTS IN CIPROFLOXACIN TABLETS AT THE END OF THIS MEDICATION GUIDE.
- ALSO TAKE A MEDICINE CALLED TIZANIDINE (ZANAFLEX®). SERIOUS SIDE EFFECTS FROM TIZANIDINE ARE LIKELY TO HAPPEN.

What should I tell my healthcare provider before taking ciprofloxacin tablets?

SEE “WHAT IS THE MOST IMPORTANT INFORMATION I SHOULD KNOW ABOUT CIPROFLOXACIN TABLETS?”

Tell your healthcare provider about all your medical conditions, including if you:

- have tendon problems
- have a disease that causes muscle weakness (myasthenia gravis)
- have central nervous system problems (such as epilepsy)
- have nerve problems
- have or anyone in your family has an irregular heartbeat, especially a condition called “QT prolongation”
- have a history of seizures
- have kidney problems. You may need a lower dose of ciprofloxacin tablets if your kidneys do not work well.
- have rheumatoid arthritis (RA) or other history of joint problems
- have trouble swallowing pills
- are pregnant or planning to become pregnant. It is not known if ciprofloxacin tablets will harm your unborn child.
- are breast-feeding or planning to breast-feed. Ciprofloxacin tablets passes into breast milk. You and your healthcare provider should decide whether you will take ciprofloxacin tablets or breast-feed.

Tell your healthcare provider about all the medicines you take, including prescription and non-prescription medicines, vitamins, and herbal and dietary supplements. Ciprofloxacin tablets and other medicines can affect each other causing side effects. Especially tell your healthcare provider if you take:

- an NSAID (Non-Steroidal Anti-Inflammatory Drug). Many common medicines for pain relief are NSAIDs. Taking an NSAID while you take ciprofloxacin tablets or other fluoroquinolones may increase your risk of central nervous system effects and seizures. See “What are the possible side effects of ciprofloxacin tablets?”
- a blood thinner (warfarin, Coumadin®, Jantoven®)
- tizanidine (Zanaflex®) You should not take ciprofloxacin tablets if you are already taking tizanidine. See “Who should not take ciprofloxacin tablets?”
- theophylline (Theo-24®, Elixophyllin®, Theochron®, Uniphyl®, Theolair®)
- glyburide (Micronase®, Glynase®, Diabeta®, Glucovance®). See “What are the possible side effects of ciprofloxacin tablets?”
- phenytoin(Fosphenytoin Sodium®, Cerebyx®, Dilantin-125®, Dilantin®, Extended Phenytoin Sodium®, Prompt Penytoin Sodium®, Phenytek®)
- products that contain caffeine
- a medicine to control your heart rate or rhythm (antiarrhythmics) See “What are the possible side effects of ciprofloxacin tablets?”
- an anti-psychotic medicine
- a tricyclic antidepressant
- a water pill (diuretic)
- a steroid medicine. Corticosteroids taken by mouth or by injection may increase the chance of tendon injury. See “What is the most important information I should know about ciprofloxacin tablets?”
- methotrexate (Trexall®)
- Probenecid (Probalan®, Col-probenecid®)
- Metoclopromide (Reglan®, Reglan ODT®)
- Certain medicines may keep ciprofloxacin tablets from working correctly. Take ciprofloxacin tablets either 2 hours before or 6 hours after taking these products:
  - an antacid, multivitamin, or other product that has magnesium, calcium, aluminum, iron, or zinc
  - sucralfate (Carafate®)
  - didanosine (Videx®, Videx® EC).

Ask your healthcare provider if you are not sure if any of your medicines are listed above.

KNOW THE MEDICINES YOU TAKE. KEEP A LIST OF YOUR MEDICINES AND SHOW IT TO YOUR HEALTHCARE PROVIDER AND PHARMACIST WHEN YOU GET A NEW MEDICINE.

How should I take ciprofloxacin tablets?

- Take ciprofloxacin tablets exactly as prescribed by your healthcare provider.
- Take ciprofloxacin tablets in the morning and evening at about the same time each day. Swallow the tablet whole. Do not split, crush or chew the tablet. Tell your healthcare provider if you cannot swallow the tablet whole.
- Take ciprofloxacin extended-release tablets one time each day at about the same time each day. Swallow the tablet whole. Do not split, crush or chew the tablet. Tell your healthcare provider if you cannot swallow the tablet whole.
- Ciprofloxacin tablets can be taken with or without food.
- Ciprofloxacin tablets should not be taken with dairy products (like milk or yogurt) or calcium-fortified juices alone, but may be taken with a meal that contains these products.
- Drink plenty of fluids while taking ciprofloxacin tablets.
- Do not skip any doses, or stop taking ciprofloxacin tablets even if you begin to feel better, until you finish your prescribed treatment, unless:
  - you have tendon effects (see “What is the most important information I should know about ciprofloxacin tablets?”),
  - you have a serious allergic reaction (see “What are the possible side effects of ciprofloxacin tablets?”), or
  - your healthcare provider tells you to stop.

This will help make sure that all of the bacteria are killed and lower the chance that the bacteria will become resistant to ciprofloxacin tablets. If this happens, ciprofloxacin tablets and other antibiotic medicines may not work in the future.

- If you miss a dose of ciprofloxacin tablets, take it as soon as you remember. Do not take two doses at the same time, and do not take more than two doses in one day.
- If you miss a dose of ciprofloxacin extended-release tablets, take it as soon as you remember. Do not take more than one dose in one day.
- If you take too much, call your healthcare provider or get medical help immediately.

If you have been prescribed ciprofloxacin tablets after being exposed to anthrax:

- Ciprofloxacin tablets has been approved to lessen the chance of getting anthrax disease or worsening of the disease after you are exposed to the anthrax bacteria germ.
- Take ciprofloxacin tablets exactly as prescribed by your healthcare provider. Do not stop taking ciprofloxacin tablets without talking with your healthcare provider. If you stop taking ciprofloxacin tablets too soon, it may not keep you from getting the anthrax disease.
- Side effects may happen while you are taking ciprofloxacin tablets. When taking your ciprofloxacin tablets to prevent anthrax infection, you and your healthcare provider should talk about whether the risks of stopping ciprofloxacin tablets too soon are more important than the risks of side effects with ciprofloxacin tablets.
- If you are pregnant, or plan to become pregnant while taking ciprofloxacin tablets, you and your healthcare provider should decide whether the benefits of taking ciprofloxacin tablets for anthrax are more important than the risks.

What should I avoid while taking ciprofloxacin tablets?

- Ciprofloxacin tablets can make you feel dizzy and lightheaded. Do not drive, operate machinery, or do other activities that require mental alertness or coordination until you know how ciprofloxacin tablets affects you.
- Avoid sunlamps, tanning beds, and try to limit your time in the sun. Ciprofloxacin tablets can make your skin sensitive to the sun (photosensitivity) and the light from sunlamps and tanning beds. You could get severe sunburn, blisters or swelling of your skin. If you get any of these symptoms while taking ciprofloxacin tablets, call your healthcare provider right away. You should use a sunscreen and wear a hat and clothes that cover your skin if you have to be in sunlight.

What are the possible side effects of ciprofloxacin tablets?

Ciprofloxacin tablets can cause side effects that may be serious or even cause death. See “What is the most important information I should know about ciprofloxacin tablets?”

OTHER SERIOUS SIDE EFFECTS OF CIPROFLOXACIN TABLETS INCLUDE:

- Central Nervous System Effects

Seizures have been reported in people who take fluoroquinolone antibiotics including ciprofloxacin tablets. Tell your healthcare provider if you have a history of seizures. Ask your healthcare provider whether taking ciprofloxacin tablets will change your risk of having a seizure.

CENTRAL NERVOUS SYSTEM (CNS) SIDE EFFECTS MAY HAPPEN AS SOON AS AFTER TAKING THE FIRST DOSE OF CIPROFLOXACIN TABLETS. TALK TO YOUR HEALTHCARE PROVIDER RIGHT AWAY IF YOU GET ANY OF THESE SIDE EFFECTS, OR OTHER CHANGES IN MOOD OR BEHAVIOR:

- feel dizzy
- seizures
- hear voices, see things, or sense things that are not there (hallucinations)
- feel restless
- tremors
- feel anxious or nervous
- confusion
- depression
- trouble sleeping
- nightmares
- feel more suspicious (paranoia)
- suicidal thoughts or acts
- Serious allergic reactions
  Allergic reactions can happen in people taking fluoroquinolones, including ciprofloxacin tablets, even after only one dose. Stop taking ciprofloxacin tablets and get emergency medical help right away if you get any of the following symptoms of a severe allergic reaction:

- hives
- trouble breathing or swallowing
- swelling of the lips, tongue, face
- throat tightness, hoarseness
- rapid heartbeat
- faint
- yellowing of the skin or eyes. Stop taking ciprofloxacin tablets and tell your healthcare provider right away if you get yellowing of your skin or white part of your eyes, or if you have dark urine. These can be signs of a serious reaction to ciprofloxacin tablets (a liver problem).

- Skin rash
  Skin rash may happen in people taking ciprofloxacin tablets, even after only one dose. Stop taking ciprofloxacin tablets at the first sign of a skin rash and call your healthcare provider. Skin rash may be a sign of a more serious reaction to ciprofloxacin tablets.

- Serious heart rhythm changes (QT prolongation and torsades de pointes)Tell your healthcare provider right away if you have a change in your heart beat (a fast or irregular heartbeat), or if you faint. Ciprofloxacin tablets may cause a rare heart problem known as prolongation of the QT interval. This condition can cause an abnormal heartbeat and can be very dangerous. The chances of this event are higher in people:
  - who are elderly
  - with a family history of prolonged QT interval,
  - with low blood potassium (hypokalemia),
  - who take certain medicines to control heart rhythm (antiarrhythmics).
- Intestine infection (Pseudomembranous colitis)Pseudomembranous colitis can happen with most antibiotics, including ciprofloxacin tablets. Call your healthcare provider right away if you get watery diarrhea, diarrhea that does not go away, or bloody stools. You may have stomach cramps and a fever. Pseudomembranous colitis can happen 2 or more months after you have finished your antibiotic.
- Changes in sensation and possible nerve damage (Peripheral Neuropathy)Damage to the nerves in arms, hands, legs, or feet can happen in people who take fluoroquinolones, including ciprofloxacin tablets. Talk with your healthcare provider right away if you get any of the following symptoms of peripheral neuropathy in your arms, hands, legs, or feet:
  - pain
  - burning
  - tingling
  - numbness
  - weakness

CIPROFLOXACIN TABLETS MAY NEED TO BE STOPPED TO PREVENT PERMANENT NERVE DAMAGE.

- Low blood sugar (hypoglycemia)
  People who take ciprofloxacin tablets and other fluoroquinolone medicines with the oral anti-diabetes medicine glyburide (Micronase, Glynase, Diabeta, Glucovance) can get low blood sugar (hypoglycemia) which can sometimes be severe. Tell your healthcare provider if you get low blood sugar with ciprofloxacin tablets. Your antibiotic medicine may need to be changed.
- Sensitivity to sunlight (photosensitivity)
  See “What should I avoid while taking ciprofloxacin tablets?”
- Joint Problems
  Increased chance of problems with joints and tissues around joints in children under 18 years old. Tell your child’s healthcare provider if your child has any joint problems during or after treatment with ciprofloxacin tablets.

THE MOST COMMON SIDE EFFECTS OF CIPROFLOXACIN TABLETS INCLUDE:

- nausea
- headache
- diarrhea
- vomiting
- vaginal yeast infection
- changes in liver function tests
- pain or discomfort in the abdomen

THESE ARE NOT ALL THE POSSIBLE SIDE EFFECTS OF CIPROFLOXACIN TABLETS. TELL YOUR HEALTHCARE PROVIDER ABOUT ANY SIDE EFFECT THAT BOTHERS YOU, OR THAT DOES NOT GO AWAY.

CALL YOUR DOCTOR FOR MEDICAL ADVICE ABOUT SIDE EFFECTS. YOU MAY REPORT SIDE EFFECTS TO FDA AT 1-800-FDA-1088.

How should I store ciprofloxacin tablets?

- Ciprofloxacin Tablets:
  - Store ciprofloxacin tablets below 86°F (30°C).

- Ciprofloxacin Extended-Release Tablets:
  - Store ciprofloxacin extended-release tablets at 20°-25°C (68°-77°F); excursions permitted to 15°-30°C (59°-86°F) [see USP Controlled Room Temperature].

KEEP CIPROFLOXACIN TABLETS AND ALL MEDICINES OUT OF THE REACH OF CHILDREN.

GENERAL INFORMATION ABOUT CIPROFLOXACIN TABLETS

MEDICINES ARE SOMETIMES PRESCRIBED FOR PURPOSES OTHER THAN THOSE LISTED IN A MEDICATION GUIDE. DO NOT USE CIPROFLOXACIN TABLETS FOR A CONDITION FOR WHICH IT IS NOT PRESCRIBED. DO NOT GIVE CIPROFLOXACIN TABLETS TO OTHER PEOPLE, EVEN IF THEY HAVE THE SAME SYMPTOMS THAT YOU HAVE. IT MAY HARM THEM.

THIS MEDICATION GUIDE SUMMARIZES THE MOST IMPORTANT INFORMATION ABOUT CIPROFLOXACIN TABLETS. IF YOU WOULD LIKE MORE INFORMATION ABOUT CIPROFLOXACIN TABLETS, TALK WITH YOUR HEALTHCARE PROVIDER. YOU CAN ASK YOUR HEALTHCARE PROVIDER OR PHARMACIST FOR INFORMATION ABOUT CIPROFLOXACIN TABLETS THAT IS WRITTEN FOR HEALTHCARE PROFESSIONALS. FOR MORE INFORMATION CALL 1-888-375-3784.

What are the ingredients in ciprofloxacin tablets?

- Ciprofloxacin Tablets:
  - Active ingredient: ciprofloxacin
  - Inactive ingredients: colloidal silicon dioxide, hypromellose, magnesium stearate, microcrystalline cellulose, polyethylene glycol 400, sodium starch glycolate, corn starch and titanium dioxide.

- Ciprofloxacin Extended-Release Tablets:
  - Active ingredient: ciprofloxacin
  - Inactive ingredients: crospovidone, colloidal silicon dioxide, ethylcellulose, hypromellose, magnesium stearate, polyethylene glycol, succinic acid and titanium dioxide

To reorder additional medguides, please contact Dr. Reddy’s Customer Service at 1-866-733-3952.

This Medication Guide has been approved by the U.S. Food and Drug Administration.

Rx Only

Manufactured by:

Dr. Reddy’s Laboratories Limited

Bachepalli – 502 325 INDIA

Rx Only

Manufactured by:
Dr. Reddy's Laboratories Limited
Bachepalli – 502 325 INDIA

Revised:0811

PACKAGE LABEL.PRINCIPAL DISPLAY PANEL SECTION

500 mg Labels

Container label

Carton Label

1000 mg Labels

Container label

Carton Label